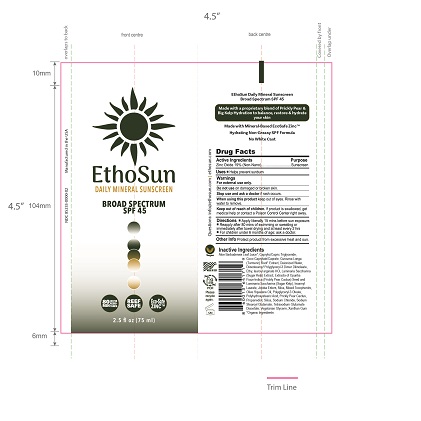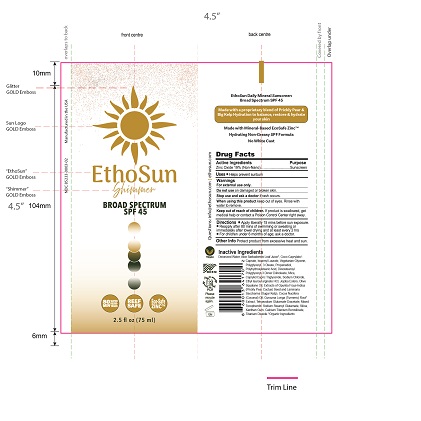 DRUG LABEL: EthoSun Shimmer Daily Mineral Sunscreen Broad Spectrum SPF 45
NDC: 85233-0003 | Form: CREAM
Manufacturer: EthoSun, Inc
Category: otc | Type: HUMAN OTC DRUG LABEL
Date: 20250603

ACTIVE INGREDIENTS: ZINC OXIDE 0.19 g/1 [arb'U]
INACTIVE INGREDIENTS: ALOE BARBADENSIS LEAF JUICE; CAPRYLIC/CAPRIC TRIGLYCERIDE; COCO-CAPRYLATE/CAPRATE; CURCUMA LONGA (TURMERIC) ROOT; WATER; DIISOSTEAROYL POLYGLYCERYL-3 DIMER DILINOLEATE; ETHYL LAUROYL ARGINATE HYDROCHLORIDE; OPUNTIA FICUS-INDICA SEED OIL; ISOAMYL LAURATE; HYDROLYZED JOJOBA ESTERS; MICA; TOCOPHEROL; SQUALENE; POLYGLYCERYL-3 OLEATE; POLYHYDROXYSTEARIC ACID (2300 MW); PRICKLY PEAR FRUIT; PROPANEDIOL; SILICA; SODIUM CHLORIDE; SODIUM STEAROYL GLUTAMATE; TETRASODIUM GLUTAMATE DIACETATE; GLYCERIN; XANTHAN GUM; COCOS NUCIFERA (COCONUT) OIL; TITANIUM DIOXIDE

Do not Use

On damaged or broken skin.

Stop use and ask doctor

if rash occurs.

Directions

- Apply liberally 15 mins before aun exposure.
- Reapply after 80 mins of swimming or sweating or immediately after towel drying and at least evary 2 hrs.
- For children under 6 months of age; ask doctor.

Other Info

Protect product from excessive heat and sun.

Purpose:

Sunscreen

Keep out of reach of children.

If product is swallowed, get medical help or contact a Poison Control Center right away.

Uses:

Helps prevent sunburn.

Directions:

- Apply liberally 15 minutes before sun exposure.
- Reapply:
- After 80 minutes of swimming or sweating
- Immediately after towel drying
- At least every 2 hours
- For children under 6 months of age: ask a doctor.

Inactive Ingredients:

Deionized Water, Aloe Barbadensis Leaf Juice*, Coco-Caprylate/Caprate, Caprylic/Capric Triglyceride, Glycerin*, Butyloctyl Salicylate, Isopropyl Lauroyl Sarcosinate, Lauryl Glucoside, Polyglyceryl-3 Caprate, Polyhydroxystearic Acid, Polyhydroxystearic Acid, Diisostearoyl Polyglyceryl-3 Dimer Dilinoleate, Magnesium Sulfate, Cetearyl Alcohol, Polyglyceryl-10 Oleate, Polyhydroxystearic Acid, Stearalkonium Hectorite, Sodium Chloride, Tocopherol (Vitamin E), Helianthus Annuus (Sunflower) Seed Oil*, Opuntia Ficus-Indica (Prickly Pear) Extract*, Macrocystis Pyrifera (Kelp) Extract*, Cucumis Sativus (Cucumber) Fruit Extract, Camellia Sinensis (Green Tea) Extract*, Euterpe Oleracea (Acai) Fruit Extract*, Cucurbita Pepo (Pumpkin) Seed Extract*, Sodium Dehydroacetate, Ethylhexylglycerin, Sodium Gluconate, Citric Acid, Sodium Citrate, Potassium Sorbate, Sodium Benzoate, Fragrance**, Iron Oxide (CI 77491), Mica, Titanium Dioxide

*Organic Ingredients

Warnings:

For external use only.

Do not use on damaged or broken skin.

Stop use and ask a doctor if rash occurs.

When using this product keep out of eyes. Rinse with water to remove.

Keep out of reach of children. If product is swallowed, get medical help or contact a Poison Control Center right away.